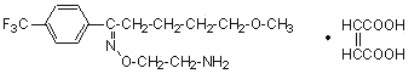 DRUG LABEL: Unknown
Manufacturer: Synthon Pharmaceuticals, Inc.
Category: prescription | Type: HUMAN PRESCRIPTION DRUG LABELING
Date: 20070920

Fluvoxamine Maleate Tablets

25 mg, 50 mg and 100 mg

Suicidality and Antidepressant Drugs

Antidepressants increased the risk compared to placebo of suicidal thinking and behavior (suicidality) in children, adolescents, and young adults in short-term studies of major depressive disorder (MDD) and other psychiatric disorders. Anyone considering the use of Fluvoxamine Maleate or any other antidepressant in a child, adolescent, or young adult must balance this risk with the clinical need. Short-term studies did not show an increase in the risk of suicidality with antidepressants compared to placebo in adults beyond age 24; there was a reduction in risk with antidepressants compared to placebo in adults aged 65 and older. Depression and certain other psychiatric disorders are themselves associated with increases in the risk of suicide. Patients of all ages who are started on antidepressant therapy should be monitored appropriately and observed closely for clinical worsening, suicidality, or unusual changes in behavior. Families and caregivers should be advised of the need for close observation and communication with the prescriber. Fluvoxamine is not approved for use in pediatric patients except for patients with obsessive compulsive disorder (OCD). (See Warnings and Precautions: Pediatric Use.) (See Warnings: Clinical Worsening and Suicide Risk, Precautions: Information for Patients, and Precautions: Pediatric Use)

DESCRIPTION

Fluvoxamine maleate is a selective serotonin (5-HT) reuptake inhibitor (SSRI) belonging to a new chemical series, the 2-aminoethyl oxime ethers of aralkylketones. It is chemically unrelated to other SSRIs and clomipramine. It is chemically designated as 5-methoxy-4'-(trifluoromethyl)valerophenone-(E)-O-(2-aminoethyl)oxime maleate (1:1) and has the empirical formula C15H21O2N2F3 • C4H4O4. Its molecular weight is 434.4.

The structural formula is:

Fluvoxamine maleate is a white or off white, odorless, crystalline powder which is sparingly soluble in water, freely soluble in ethanol and chloroform and practically insoluble in diethyl ether.

Fluvoxamine Maleate Tablets are available in 25 mg, 50 mg and 100 mg strengths for oral administration. In addition to the active ingredient, fluvoxamine maleate, each tablet contains the following inactive ingredients: hypromellose, mannitol, polyethylene glycol, pregelatinized starch (corn), colloidal silicon dioxide, sodium stearyl fumarate, starch (corn), titanium dioxide and talc.

CLINICAL PHARMACOLOGY

Pharmacodynamics

The mechanism of action of fluvoxamine maleate in Obsessive Compulsive Disorder is presumed to be linked to its specific serotonin reuptake inhibition in brain neurons. In preclinical studies, it was found that fluvoxamine inhibited neuronal uptake of serotonin.

In in vitro studies fluvoxamine maleate had no significant affinity for histaminergic, alpha or beta adrenergic, muscarinic, or dopaminergic receptors. Antagonism of some of these receptors is thought to be associated with various sedative, cardiovascular, anticholinergic, and extrapyramidal effects of some psychotic drugs.

Pharmacokinetics

Bioavailability

The absolute bioavailability of fluvoxamine maleate is 53%. Oral bioavailability is not significantly affected by food.

In a dose proportionality study involving fluvoxamine maleate at 100, 200 and 300 mg/day for 10 consecutive days in 30 normal volunteers, steady state was achieved after about a week of dosing. Maximum plasma concentrations at steady state occurred within 3-8 hours of dosing and reached concentrations averaging 88, 283 and 546 ng/mL, respectively.

Thus, fluvoxamine had nonlinear pharmacokinetics over this dose range, i.e., higher doses of fluvoxamine maleate produced disproportionately higher concentrations than predicted from the lower dose.

Distribution/Protein Binding

The mean apparent volume of distribution for fluvoxamine is approximately 25 L/kg, suggesting extensive tissue distribution.

Approximately 80% of fluvoxamine is bound to plasma protein, mostly albumin, over a concentration range of 20 to 2000 ng/mL.

Metabolism

Fluvoxamine maleate is extensively metabolized by the liver; the main metabolic routes are oxidative demethylation and deamination. Nine metabolites were identified following a 5 mg radiolabelled dose of fluvoxamine maleate, constituting approximately 85% of the urinary excretion products of fluvoxamine. The main human metabolite was fluvoxamine acid which, together with its N- acetylated analog, accounted for about 60% of the urinary excretion products. A third metabolite, fluvoxethanol, formed by oxidative deamination, accounted for about 10%.

Fluvoxamine acid and fluvoxethanol were tested in an in vitro assay of serotonin and norepinephrine reuptake inhibition in rats; they were inactive except for a weak effect of the former metabolite on inhibition of serotonin uptake (1-2 orders of magnitude less potent than the parent compound). Approximately 2% of fluvoxamine was excreted in urine unchanged. (See PRECAUTIONS-Drug Interactions)

Elimination

Following a ^14C-labelled oral dose of fluvoxamine maleate (5 mg), an average of 94% of drug-related products was recovered in the urine within 71 hours.

The mean plasma half-life of fluvoxamine at steady state after multiple oral doses of 100 mg/day in healthy, young volunteers was 15.6 hours.

Elderly Subjects

In a study of Fluvoxamine Maleate Tablets at 50 and 100 mg comparing elderly (ages 66-73) and young subjects (ages 19-35), mean maximum plasma concentrations in the elderly were 40% higher. The multiple dose elimination half-life of fluvoxamine was 17.4 and 25.9 hours in the elderly compared to 13.6 and 15.6 hours in the young subjects at steady state for 50 and 100 mg doses, respectively.

In elderly patients, the clearance of fluvoxamine was reduced by about 50% and, therefore, Fluvoxamine Maleate Tablets should be slowly titrated during initiation of therapy.

Pediatric Subjects

The multiple-dose pharmacokinetics of fluvoxamine were determined in male and female children (ages 6-11) and adolescents (ages 12-17). Steady-state plasma fluvoxamine concentrations were 2-3 fold higher in children than adolescents. AUC and Cmax in children were 1.5- to 2.7-fold higher than that in adolescents (see table below). As in adults, both children and adolescents exhibited nonlinear multiple-dose pharmacokinetics. Female children showed significantly higher AUC (0-12) and Cmax compared to male children and, therefore, lower doses of Fluvoxamine Maleate Tablets may produce therapeutic benefit (see table below). No gender differences were observed in adolescents. Steady-state plasma fluvoxamine concentrations were similar in adults and adolescents at a dose of 300 mg/day, indicating that fluvoxamine exposure was similar in these two populations (see table below). Dose adjustment in adolescents (up to the adult maximum dose of 300 mg) may be indicated to achieve therapeutic benefit.

Comparison of Mean (SD) fluvoxamine pharmacokinetic parameters between children, adolescents and adults
Pharmacokinetic Parameter (Body weight corrected) | Dose=200 mg/day (100 mg/day bid) |  | Dose=300 mg/day (150 mg bid)
Pharmacokinetic Parameter (Body weight corrected) | Children (n=10) | Adolescent (n=17) | Adolescents (n=13) | Adults (n=16)
AUC0-12 (ng ∙ h/ml/kg) | 155.1 (160.9) | 43.9 (27.9) | 69.6 (46.6) | 59.4 (40.9)
Cmax (ng/ml/kg) | 14.8 (14.9) | 4.2 (2.6) | 6.7 (4.2) | 5.7 (3.9)
Cmin (ng/ml/kg) | 11.0 (11.9) | 2.9 (2.0) | 4.8 (3.8) | 4.6 (3.2)

Comparison of Mean (SD) fluvoxamine pharmacokinetic parameters between male and female children (6-11 years)
Pharmacokinetic Parameter (Body weight corrected) | Dose =200 mg/day (100 mg bid)
Pharmacokinetic Parameter (Body weight corrected) | Male children (n=7) | Female children (n=3)
AUC0-12 (ng ∙ h/ml/kg) | 95.8 (83.9) | 293.5 (233.0)
Cmax (ng/ml/kg) | 9.1 (7.6) | 28.1 (21.1)
Cmin (ng/ml/kg) | 6.6 (6.1) | 21.2 (17.6)

Hepatic and Renal Disease

A cross study comparison (healthy subjects vs. patients with hepatic dysfunction) suggested a 30% decrease in fluvoxamine clearance in association with hepatic dysfunction. The mean minimum plasma concentrations in renally impaired patients (creatinine clearance of 5 to 45 mL/min) after 4 and 6 weeks of treatment (50 mg bid, N=13) were comparable to each other, suggesting no accumulation of fluvoxamine in these patients. (See PRECAUTIONS-Use in Patients with Concomitant Illness)

Clinical Trials

Adult OCD Studies

The effectiveness of Fluvoxamine Maleate Tablets for the treatment of Obsessive Compulsive Disorder (OCD) was demonstrated in two 10-week multicenter, parallel group studies of adult outpatients. Patients in these trials were titrated to a total daily fluvoxamine maleate dose of 150 mg/day over the first two weeks of the trial, following which the dose was adjusted within a range of 100-300 mg/day (on a bid schedule), on the basis of response and tolerance. Patients in these studies had moderate to severe OCD (DSM-III-R), with mean baseline ratings on the Yale-Brown Obsessive Compulsive Scale (Y-BOCS), total score of 23. Patients receiving fluvoxamine maleate experienced mean reductions of approximately 4 to 5 units on the Y-BOCS total score, compared to a 2 unit reduction for placebo patients.

The following table provides the outcome classification by treatment group on the Global Improvement item of the Clinical Global Impressions (CGI) scale for both studies combined.

OUTCOME CLASSIFICATION (%) ON CGI-GLOBAL IMPROVEMENT ITEM FOR COMPLETERS IN POOL OF TWO ADULT OCD STUDIES
Outcome Classification | Fluvoxamine (N = 120) | Placebo (N = 134)
Very Much Improved | 13% | 2%
Much Improved | 30% | 10%
Minimally Improved | 22% | 32%
No Change | 31% | 51%
Worse | 4% | 6%

Exploratory analyses for age and gender effects on outcomes did not suggest any differential responsiveness on the basis of age or sex.

Pediatric OCD Study

The effectiveness of Fluvoxamine Maleate Tablets for the treatment of OCD was also demonstrated in a 10-week multicenter, parallel group study in a pediatric outpatient population (children and adolescents, ages 8-17). Patients in this study were titrated to a total daily fluvoxamine maleate dose of approximately 100 mg/day over the first two weeks of the trial, following which the dose was adjusted within a range of 50-200 mg/day (on a bid schedule) on the basis of response and tolerance. All patients had moderate-to-severe OCD (DSM-III-R) with mean baseline ratings on the Children's Yale-Brown Obsessive Compulsive Scale (CY-BOCS), total score of 24. Patients receiving fluvoxamine maleate experienced mean reductions of approximately 6 units on the CY-BOCS total score, compared to a 3 unit reduction for placebo patients.

The following table provides the outcome classification by treatment group on the Global Improvement item of the Clinical Global Impression (CGI) scale for the pediatric study.

OUTCOME CLASSIFICATION (%) ON CGI-GLOBAL IMPROVEMENT ITEM FOR COMPLETERS IN PEDIATRIC STUDIES
Outcome Classification | Fluvoxamine (N = 38) | Placebo (N = 36)
Very Much Improved | 21% | 11%
Much Improved | 18% | 17%
Minimally Improved | 37% | 22%
No Change | 16% | 44%
Worse | 8% | 6%

Post hoc exploratory analyses for gender effects on outcomes did not suggest any differential responsiveness on the basis of gender. Further exploratory analyses revealed a prominent treatment effect in the 8-11 age group and essentially no effect in the 12-17 age group. While the significance of these results is not clear, the 2-3 fold higher steady state plasma fluvoxamine concentrations in children compared to adolescents (see Pharmacokinetics) is suggestive that decreased exposure in adolescents may have been a factor, and dose adjustment in adolescents (up to the adult maximum of 300 mg) may be indicated to achieve therapeutic benefit.

INDICATIONS AND USAGE

Fluvoxamine Maleate Tablets are indicated for the treatment of obsessions and compulsions in patients with Obsessive Compulsive Disorder (OCD), as defined in the DSM-III-R. The obsessions or compulsions cause marked distress, are time-consuming, or significantly interfere with social or occupational functioning.

The efficacy of Fluvoxamine Maleate Tablets was established in three 10-week trials with obsessive compulsive outpatients with the diagnosis of Obsessive Compulsive Disorder as defined in DSM-III-R. (See Clinical Trials under CLINICAL PHARMACOLOGY.)

Obsessive Compulsive Disorder is characterized by recurrent and persistent ideas, thoughts, impulses or images (obsessions) that are ego- dystonic and/or repetitive, purposeful, and intentional behaviors (compulsions) that are recognized by the person as excessive or unreasonable.

The effectiveness of Fluvoxamine Maleate Tablets for long-term use, i.e., for more than 10 weeks, has not been systematically evaluated in placebo-controlled trials. Therefore, the physician who elects to use Fluvoxamine Maleate Tablets for extended periods should periodically re-evaluate the long-term usefulness of the drug for the individual patient. (See DOSAGE AND ADMINISTRATION.)

CONTRAINDICATIONS

Co-administration of thioridazine, terfenadine, astemizole, cisapride, pimozide, alosetron or tizanidine with fluvoxamine maleate is contraindicated (see WARNINGS, PRECAUTIONS, and Lotronex™ (alosetron) package insert).

Fluvoxamine maleate tablets are contraindicated in patients with a history of hypersensitivity to fluvoxamine maleate.

WARNINGS

Potential for Interaction with Monoamine Oxidase Inhibitors

In patients receiving another serotonin reuptake inhibitor drug in combination with monoamine oxidase inhibitors (MAOI), there have been reports of serious, sometimes fatal, reactions including hyperthermia, rigidity, myoclonus, autonomic instability with possible rapid fluctuations of vital signs, and mental status changes that include extreme agitation progressing to delirium and coma. These reactions have also been reported in patients who have discontinued that drug and have been started on a MAOI. Some cases presented with features resembling neuroleptic malignant syndrome. Therefore, it is recommended that Fluvoxamine Maleate Tablets not be used in combination with a MAOI, or within 14 days of discontinuing treatment with a MAOI. After stopping Fluvoxamine Maleate Tablets, at least 2 weeks should be allowed before starting a MAOI.

Potential Interaction with Thioridazine

The effect of fluvoxamine (25 mg bid for one week) on thioridazine steady-state concentrations was evaluated in 10 male inpatients with schizophrenia. Concentrations of thioridazine and its two active metabolites, mesoridazine and sulforidazine, increased threefold following co-administration of fluvoxamine.

Thioridazine administration produces a dose-related prolongation of the QTc interval, which is associated with serious ventricular arrhythmias, such as torsade de pointes-type arrhythmias, and sudden death. It is likely that this experience underestimates the degree of risk that might occur with higher doses of thioridazine. Moreover, the effect of fluvoxamine may be even more pronounced when it is administered at higher doses.

Therefore, fluvoxamine and thioridazine should not be co-administered (see CONTRAINDICATIONS and PRECAUTIONS).

Potential Terfenadine, Astemizole, Cisapride, and Pimozide Interactions

Terfenadine, astemizole, cisapride, and pimozide are all metabolized by the cytochrome P4503A4 isozyme, and it has been demonstrated that ketoconazole, a potent inhibitor of 3A4, blocks the metabolism of these drugs, resulting in increased plasma concentrations of parent drug. Increased plasma concentrations of terfenadine, astemizole, cisapride, and pimozide cause QT prolongation and have been associated with torsades de pointes-type ventricular tachycardia, sometimes fatal. As noted below, a substantial pharmacokinetic interaction has been observed for fluvoxamine in combination with alprazolam, a drug that is known to be metabolized by the 3A4 isozyme. Although, it has not been definitively demonstrated that fluvoxamine is a potent 3A4 inhibitor, it is likely to be, given the substantial interaction of fluvoxamine with alprazolam. Consequently, it is recommended that fluvoxamine not be used in combination with either terfenadine, astemizole, cisapride, or pimozide (see CONTRAINDICATIONS and PRECAUTIONS).

Potential Tizanidine Interaction

Fluvoxamine is a potent inhibitor of CYP1A2 and tizanidine is a CYP1A2 substrate. The effect of fluvoxamine (100 mg daily for 4 days) on the pharmacokinetics and pharmacodynamics of a single 4 mg dose of tizanidine has been studied in 10 healthy subjects. Tizanidine Cmax was increased approximately 12-fold (range 5-fold to 32-fold), elimination half-life was increased by almost 3-fold, and AUC increased 33-fold (range 14-fold to 103-fold). The mean maximal effect on blood pressure was a 35 mm Hg decrease in systolic blood pressure, a 20 mm Hg decrease in diastolic blood pressure, and a 4 beat/min decrease in heart rate. Drowsiness was significantly increased and performance on a psychomotor task was significantly impaired. Fluvoxamine and tizanidine should not be used together. (See Contraindications and Precautions).

Potential Alosetron Interaction

Fluvoxamine, an inhibitor of several CYP isozymes, has been shown to increase mean alosetron plasma concentrations (AUC) approximately 6-fold and prolonged the half-life by approximately 3-fold. Consequently, it is recommended that fluvoxamine not be used in combination with alosetron (See Contraindications, Precautions, and Lotronex™ (alosetron) package insert).

Clinical Worsening and Suicide Risk

Patients with major depressive disorder (MDD), both adult and pediatric, may experience worsening of their depression and/or the emergence of suicidal ideation and behavior (suicidality) or unusual changes in behavior, whether or not they are taking antidepressant medications, and this risk may persist until significant remission occurs. Suicide is a known risk of depression and certain other psychiatric disorders, and these disorders themselves are the strongest predictors of suicide. There has been a long-standing concern, however, that antidepressants may have a role in inducing worsening of depression and the emergence of suicidality in certain patients during the early phases of treatment. Pooled analyses of short-term placebo-controlled trials of antidepressant drugs (SSRIs and others) showed that these drugs increase the risk of suicidal thinking and behavior (suicidality) in children, adolescents, and young adults (ages 18-24) with major depressive disorder (MDD) and other psychiatric disorders. Short-term studies did not show an increase in the risk of suicidality with antidepressants compared to placebo in adults beyond age 24; there was a reduction with antidepressants compared to placebo in adults aged 65 and older.

The pooled analyses of placebo-controlled trials in children and adolescents with MDD, obsessive compulsive disorder (OCD), or other psychiatric disorders included a total of 24 short-term trials of 9 antidepressant drugs in over 4400 patients. The pooled analyses of placebo-controlled trials in adults with MDD or other psychiatric disorders included a total of 295 short-term trials (median duration of 2 months) of 11 antidepressant drugs in over 77,000 patients. There was considerable variation in risk of suicidality among drugs, but a tendency toward an increase in the younger patients for almost all drugs studied. There were differences in absolute risk of suicidality across the different indications, with the highest incidence in MDD. The risk differences (drug vs placebo), however, were relatively stable within age strata and across indications. These risk differences (drug-placebo difference in the number of cases of suicidality per 1000 patients treated) are provided in Table 1.

Table 1
Age Range | Drug-Placebo Difference in Number of Cases of Suicidality per 1000 Patients Treated
 | Increases Compared to Placebo
<18 | 14 additional cases
18-24 | 5 additional cases
 | Decreases Compared to Placebo
25-64 | 1 fewer case
≥65 | 6 fewer cases

No suicides occurred in any of the pediatric trials. There were suicides in the adult trials, but the number was not sufficient to reach any conclusion about drug effect on suicide.

It is unknown whether the suicidality risk extends to longer-term use, i.e., beyond several months. However, there is substantial evidence from placebo-controlled maintenance trials in adults with depression that the use of antidepressants can delay the recurrence of depression.

All patients being treated with antidepressants for any indication should be monitored appropriately and observed closely for clinical worsening, suicidality, and unusual changes in behavior, especially during the initial few months of a course of drug therapy, or at times of dose changes, either increases or decreases.

The following symptoms, anxiety, agitation, panic attacks, insomnia, irritability, hostility, aggressiveness, impulsivity, akathisia (psychomotor restlessness), hypomania, and mania, have been reported in adult and pediatric patients being treated with antidepressants for major depressive disorder as well as for other indications, both psychiatric and nonpsychiatric. Although a causal link between the emergence of such symptoms and either the worsening of depression and/or the emergence of suicidal impulses has not been established, there is concern that such symptoms may represent precursors to emerging suicidality.

Consideration should be given to changing the therapeutic regimen, including possibly discontinuing the medication, in patients whose depression is persistently worse, or who are experiencing emergent suicidality or symptoms that might be precursors to worsening depression or suicidality, especially if these symptoms are severe, abrupt in onset, or were not part of the patient's presenting symptoms.

If the decision has been made to discontinue treatment, medication should be tapered, as rapidly as is feasible, but with recognition that abrupt discontinuation can be associated with certain symptoms (see PRECAUTIONS and DOSAGE AND ADMINISTRATION - Discontinuation of Treatment with Fluvoxamine Maleate Tablets, for a description of the risks of discontinuation of Fluvoxamine Maleate Tablets).

Families and caregivers of patients being treated with antidepressants for major depressive disorder or other indications, both psychiatric and nonpsychiatric, should be alerted about the need to monitor patients for the emergence of agitation, irritability, unusual changes in behavior, and the other symptoms described above, as well as the emergence of suicidality, and to report such symptoms immediately to health care providers. Such monitoring should include daily observation by families and caregivers. Prescriptions for Fluvoxamine Maleate Tablets should be written for the smallest quantity of tablets consistent with good patient management, in order to reduce the risk of overdose.

Screening Patients for Bipolar Disorder

A major depressive episode may be the initial presentation of bipolar disorder. It is generally believed (though not established in controlled trials) that treating such an episode with an antidepressant alone may increase the likelihood of precipitation of a mixed/manic episode in patients at risk for bipolar disorder. Whether any of the symptoms described above represent such a conversion is unknown. However, prior to initiating treatment with an antidepressant, patients with depressive symptoms should be adequately screened to determine if they are at risk for bipolar disorder; such screening should include a detailed psychiatric history, including a family history of suicide, bipolar disorder, and depression. It should be noted that Fluvoxamine Maleate is not approved for use in treating bipolar depression.

Other Potentially Important Drug Interactions

(Also see PRECAUTIONS - Drug Interactions)

Benzodiazepines

Benzodiazepines metabolized by hepatic oxidation (e.g., alprazolam, midazolam, triazolam, etc.) should be used with caution because the clearance of these drugs is likely to be reduced by fluvoxamine. The clearance of benzodiazepines metabolized by glucuronidation (e.g., lorazepam, oxazepam, temazepam) is unlikely to be affected by fluvoxamine.

Alprazolam

When fluvoxamine maleate (100 mg qd) and alprazolam (1 mg qid) were co-administered to steady state, plasma concentrations and other pharmacokinetic parameters (AUC, Cmax, T1/2) of alprazolam were approximately twice those observed when alprazolam was administered alone; oral clearance was reduced by about 50%. The elevated plasma alprazolam concentrations resulted in decreased psychomotor performance and memory.

This interaction, which has not been investigated using higher doses of fluvoxamine, may be more pronounced if a 300 mg daily dose is co-administered, particularly since fluvoxamine exhibits non-linear pharmacokinetics over the dosage range 100-300 mg.

If alprazolam is co-administered with Fluvoxamine Maleate Tablets, the initial alprazolam dosage should be at least halved and titration to the lowest effective dose is recommended. No dosage adjustment is required for Fluvoxamine Maleate Tablets.

Diazepam

The co-administration of Fluvoxamine Maleate Tablets and diazepam is generally not advisable. Because fluvoxamine reduces the clearance of both diazepam and its active metabolite, N-desmethyldiazepam, there is a strong likelihood of substantial accumulation of both species during chronic co-administration.

Evidence supporting the conclusion that it is inadvisable to co-administer fluvoxamine and diazepam is derived from a study in which healthy volunteers taking 150 mg/day of fluvoxamine were administered a single oral dose of 10 mg of diazepam. In these subjects (N=8), the clearance of diazepam was reduced by 65% and that of N-desmethyldiazepam to a level that was too low to measure over the course of the 2 week long study.

It is likely that this experience significantly underestimates the degree of accumulation that might occur with repeated diazepam administration. Moreover, as noted with alprazolam, the effect of fluvoxamine may even be more pronounced when it is administered at higher doses. Accordingly, diazepam and fluvoxamine should not ordinarily be co-administered.

Mexiletine

The effect of steady-state fluvoxamine (50 mg BID for 7 days) on the single dose pharmacokinetics of mexiletene (200 mg) was evaluated in 6 healthy Japanese males. The clearance of mexiletine was reduced by 38% following co-administration with fluvoxamine compared to mexiletene alone. If fluvoxamine and mexiletene are co-administered, serum mexiletene levels should be monitored.

Serotonin Syndrome

The development of a potentially life-threatening serotonin syndrome may occur with fluvoxamine treatment particularly with concomitant use of serotonergic drugs (including triptans) and with drugs which impair metabolism of serotonin (including MAOIs). Serotonin syndrome symptoms may include mental status changes (e.g., agitation, hallucinations, coma), autonomic instability (e.g., tachycardia, labile blood pressure, hyperthermia), neuromuscular aberrations (e.g., hyperreflexia, incoordination) and/or gastrointestinal symptoms (e.g., nausea, vomiting, diarrhea).

The concomitant use of fluvoxamine with MAOIs intended to treat depression is contraindicated (see CONTRAINDICATIONS and WARNINGS – Potential for Interaction with Monoamine Oxidase Inhibitors.)

If concomitant treatment of fluvoxamine with 5-hydroxytryptamine receptor agonist (triptan) is clinically warranted, careful observation of the patient is advised, particularly during treatment initiation and dose increases (see PRECAUTIONS – Drug Interactions).

The concomitant use of fluvoxamine with serotonin precursors (such a tryptophan) is not recommended (see PRECAUTIONS – Drug Interactions).

Neuroleptic Malignant Syndrome (NMS) or NMS-Like Events

Rare instances of neuroleptic malignant syndrome (NMS) or NMS-like events have been reported in association with fluvoxamine treatment when co-administered with antipsychotic. Additionally, a small number of such cases have been reported with fluvoxamine treatment in the absence of antipsychotic co-administration. These serious and sometimes fatal events can include hyperthermia, muscle rigidity, autonomic instability with possible rapid fluctuations of vital signs, and mental status changes. As these events may result in potentially life-threatening conditions, patients receiving this combination of therapy should be monitored for the emergence of NMS-like signs and symptoms. Treatment with fluvoxamine and any concomitant antipsychotic agent should be discontinued immediately if such event occurs and supportive symptomatic treatment should be initiated.

Theophylline

The effect of steady-state fluvoxamine (50 mg bid) on the pharmacokinetics of a single dose of theophylline (375 mg as 442 mg aminophylline) was evaluated in 12 healthy non-smoking, male volunteers. The clearance of theophylline was decreased approximately 3-fold. Therefore, if theophylline is co-administered with fluvoxamine maleate, its dose should be reduced to one third of the usual daily maintenance dose and plasma concentrations of theophylline should be monitored. No dosage adjustment is required for Fluvoxamine Maleate Tablets.

Warfarin

When fluvoxamine maleate (50 mg tid) was administered concomitantly with warfarin for two weeks, warfarin plasma concentrations increased by 98% and prothrombin times were prolonged.

Thus patients receiving oral anticoagulants and Fluvoxamine Maleate Tablets should have their prothrombin time monitored and their anticoagulant dose adjusted accordingly. No dosage adjustment is required for Fluvoxamine Maleate Tablets.

PRECAUTIONS

General

Discontinuation of Treatment with Fluvoxamine Maleate Tablets

During marketing of fluvoxamine maleate tablets and other SSRIs and SNRIs (Serotonin and Norepinephrine Reuptake Inhibitors), there have been spontaneous reports of adverse events occurring upon discontinuation of these drugs, particularly when abrupt, including the following: dysphoric mood, irritability, agitation, dizziness, sensory disturbances (e.g., paresthesias, such as electric shock sensations), anxiety, confusion, headache, lethargy, emotional lability, insomnia, and hypomania. While these events are generally self-limiting, there have been reports of serious discontinuation symptoms. Patients should be monitored for these symptoms when discontinuing treatment with Fluvoxamine Maleate Tablets. A gradual reduction in the dose rather than abrupt cessation is recommended whenever possible. If intolerable symptoms occur following a decrease in the dose or upon discontinuation of treatment, then resuming the previously prescribed dose may be considered. Subsequently, the physician may continue decreasing the dose but at a more gradual rate (see DOSAGE AND ADMINISTRATION).

Abnormal Bleeding

Published case reports have documented the occurrence of bleeding episodes in patients treated with psychotropic agents that interfere with serotonin reuptake. Subsequent epidemiological studies, both of the case-control and cohort design, have demonstrated an association between use of psychotropic drugs that interfere with serotonin reuptake and the occurrence of upper gastrointestinal bleeding. In two studies, concurrent use of a nonsteroidal anti-inflammatory drug (NSAID) or aspirin potentiated the risk of bleeding (see Drug Interactions). Although these studies focused on upper gastrointestinal bleeding, there is reason to believe that bleeding at other sites may be similarly potentiated. Patients should be cautioned regarding the risk of bleeding associated with the concomitant use of fluvoxamine with NSAIDs, aspirin, or other drugs that affect coagulation.

Activation of Mania/Hypomania

During premarketing studies involving primarily depressed patients, hypomania or mania occurred in approximately 1% of patients treated with fluvoxamine. In a 10 week pediatric OCD study, 2 out of 57 patients (4%) treated with fluvoxamine experienced manic reactions compared to none of 63 placebo patients.

Activation of mania/hypomania has also been reported in a small proportion of patients with major affective disorder who were treated with other marketed antidepressants. As with all antidepressants, Fluvoxamine Maleate Tablets should be used cautiously in patients with a history of mania.

Seizures

During premarketing studies, seizures were reported in 0.2% of fluvoxamine-treated patients. Fluvoxamine Maleate Tablets should be used cautiously in patients with a history of seizures. It should be discontinued in any patient who develops seizures.

Hyponatremia

Hyponatremia may occur as a result of treatment with SSRIs and SNRIs, including fluvoxamine. In many cases, this hyponatremia appears to be the result of the syndrome of inappropriate antidiuretic hormone secretion (SIADH). Cases with serum sodium lower than 110 mmol/L have been reported. Elderly patients may be at greater risk of developing hyponatremia with SSRIs and SNRIs. Also, patients taking diuretics or who are otherwise volume depleted may be at greater risk (see Geriatric Use). Discontinuation of fluvoxamine should be considered in patients with symptomatic hyponatremia and appropriate medical intervention should be instituted.

Signs and symptoms of hyponatremia include headache, difficulty concentrating, memory impairment, confusion, weakness, and unsteadiness, which may lead to falls. Signs and symptoms associated with more severe and/or acute cases have included hallucination, syncope, seizure, coma, respiratory arrest, and death.

Use in Patients with Concomitant Illness

Closely monitored clinical experience with Fluvoxamine Maleate Tablets in patients with concomitant systemic illness is limited. Caution is advised in administering Fluvoxamine Maleate Tablets to patients with diseases or conditions that could affect hemodynamic responses or metabolism.

Fluvoxamine Maleate Tablets have not been evaluated or used to any appreciable extent in patients with a recent history of myocardial infarction or unstable heart disease. Patients with these diagnoses were systematically excluded from many clinical studies during the product's premarketing testing. Evaluation of the electrocardiograms for patients with depression or OCD who participated in premarketing studies revealed no differences between fluvoxamine and placebo in the emergence of clinically important ECG changes.

In patients with liver dysfunction, fluvoxamine clearance was decreased by approximately 30%. Fluvoxamine Maleate Tablets should be slowly titrated in patients with liver dysfunction during the initiation of treatment.

Information for Patients

Prescribers or other health professionals should inform patients, their families, and their caregivers about the benefits and risks associated with treatment with Fluvoxamine Maleate Tablets and should counsel them in its appropriate use. A patient Medication Guide about "Antidepressant Medicines, Depression and other Serious Mental Illness, and Suicidal Thoughts or Actions" is available for Fluvoxamine Maleate Tablets. The prescriber or health professional should instruct patients, their families, and their caregivers to read the Medication Guide and should assist them in understanding its contents. Patients should be given the opportunity to discuss the contents of the Medication Guide and to obtain answers to any questions they may have. The complete text of the Medication Guide is reprinted at the end of this document.

Patients should be advised of the following issues and asked to alert their prescriber if these occur while taking Fluvoxamine Maleate Tablets.

Patients should be cautioned about the risk of serotonin syndrome with the concomitant use of fluvoxamine and triptans, tramadol or other serotonergic agents.

Clinical Worsening and Suicidal Risk

Patients, their families, and their caregivers should be encouraged to be alert to the emergence of anxiety, agitation, panic attacks, insomnia, irritability, hostility, aggressiveness, impulsivity, akathisia (psychomotor restless), hypomania, mania, other unusual changes in behavior, worsening of depression, and suicidal ideation, especially early during antidepressant treatment and when the dose is adjusted up or down. Families and caregivers of patients should be advised to look for the emergence of such symptoms on a day-to-day basis, since changes may be abrupt. Such symptoms should be reported to the patient's prescriber or health professional, especially if they are severe, abrupt in onset, or were not part of the patient's presenting symptoms. Symptoms such as these may be associated with an increased risk for suicidal thinking and behavior and indicate a need for very close monitoring and possibly changes in the medication.

Interference with Cognitive or Motor Performance

Since any psychoactive drug may impair judgement, thinking, or motor skills, patients should be cautioned about operating hazardous machinery, including automobiles, until they are certain that fluvoxamine maleate tablet therapy does not adversely affect their ability to engage in such activities.

Pregnancy

Patients should be advised to notify their physicians if they become pregnant or intend to become pregnant during therapy with Fluvoxamine Maleate Tablets.

Nursing

Patients receiving Fluvoxamine Maleate Tablets should be advised to notify their physicians if they are breast feeding an infant. (See PRECAUTIONS - Nursing Mothers)

Concomitant Medication

Patients should be advised to notify their physicians if they are taking, or plan to take, any prescription or over-the-counter drugs, since there is a potential for clinically important interactions with Fluvoxamine Maleate Tablets. Patients should be cautioned about the concomitant use of fluvoxamine and NSAIDs, aspirin, or other drugs that affect coagulation since the combined use of psychotropic drugs that interfere with serotonin reuptake and these agents has been associated with an increased risk of bleeding.

Because of the potential for the increased risk of serious adverse reactions including severe lowering of blood pressure and sedation when fluvoxamine and tizanidine are used together, fluvoxamine should not be used with tizanidine.

Because of the potential for the increased risk of serious adverse reactions when fluvoxamine and alosetron are used together, fluvoxamine should not be used with Lotronex™ (alosetron).

Alcohol

As with other psychotropic medications, patients should be advised to avoid alcohol while taking Fluvoxamine Maleate Tablets.

Allergic Reactions

Patients should be advised to notify their physicians if they develop a rash, hives, or a related allergic phenomenon during therapy with Fluvoxamine Maleate Tablets.

Laboratory Tests

There are no specific laboratory tests recommended.

Drug interactions

Potential Interactions with Drugs that Inhibit or are Metabolized by Cytochrome P450 Isozymes

Multiple hepatic cytochrome P450 (CYP450) enzymes are involved in the oxidative biotransformation of a large number of structurally different drugs and endogenous compounds. The available knowledge concerning the relationship of fluvoxamine and the CYP450-enzyme system has been obtained mostly from pharmacokinetic interaction studies conducted in healthy volunteers, but some preliminary in vitro data are also available.

Based on a finding of substantial interactions of fluvoxamine with certain of these drugs (see later parts of this section and also WARNINGS for details) and limited in vitro data for the 3A4 isozyme, it appears that fluvoxamine inhibits the following isozymes that are known to be involved in the metabolism of the listed drugs:

1A2 | 2C9 | 3A4 | 2C19
Warfarin | Warfarin | Alprazolam | Omeprazole
Theophylline
Propranolol
Tizanidine

In vitro data suggest that fluvoxamine is a relatively weak inhibitor of the 2D6 isozyme.

Approximately 7% of the normal population has a genetic defect that leads to reduced levels of activity of the cytochrome P4502D6 isozyme. Such individuals have been referred to as "poor metabolizers" (PM) of drugs such as debrisoquin, dextromethorphan, and tricyclic antidepressants. While none of the drugs studied for drug interactions significantly affected the pharmacokinetics of fluvoxamine, an in vivo study of fluvoxamine single- dose pharmokinetics in 13 PM subjects demonstrated altered pharmokinetic properties compared to 16 "extensive metabolizers" (EM): mean Cmax, AUC, and half-life were increased by 52%, 200%, and 62%, respectively, in the PM compared to the EM group. This suggests that fluvoxamine is metabolized, at least in part, by the 2D6 isozyme. Caution is indicated in patients known to have reduced levels of P4502D6 activity and those receiving concomitant drugs known to inhibit this isozyme (e.g. quinidine).

The metabolism of fluvoxamine has not been fully characterized and the effects of potent P450 isozyme inhibition, such as the ketoconazole inhibition of 3A4, on fluvoxamine metabolism have not been studied.

A clinically significant fluvoxamine interaction is possible with drugs having a narrow therapeutic ratio such as terfenadine, astemizole, cisapride, or pimozide, warfarin, theophylline, certain benzodiazepines and phenytoin. If Fluvoxamine Maleate Tablets are to be administered together with a drug that is eliminated via oxidative metabolism and has a narrow therapeutic window, plasma levels and/or pharmacodynamic effects of the latter drug should be monitored closely, at least until steady-state conditions are reached (See CONTRAINDICATIONS and WARNINGS).

CNS Active Drugs

Alcohol

Studies involving single 40 g doses of ethanol (oral administration in one study and intravenous in the other) and multiple dosing with fluvoxamine maleate (50 mg bid) revealed no effect of either drug on the pharmacokinetics or pharmacodynamics of the other.

Alprazolam

See WARNINGS.

Antipsychotics

See WARNINGS-Other Potentially Important Drug Interactions – Neuroleptic Malignant Syndrome (NMS) or NMS-Like Events.

Diazepam

See WARNINGS.

Carbamazepine

Elevated carbamazepine levels and symptoms of toxicity have been reported with the co-administration of fluvoxamine maleate and carbamazepine.

Clozapine

Elevated serum levels of clozapine have been reported in patients taking fluvoxamine maleate and clozapine. Since clozapine related seizures and orthostatic hypotension appear to be dose related, the risk of these adverse events may be higher when fluvoxamine and clozapine are co-administered. Patients should be closely monitored when fluvoxamine maleate and clozapine are used concurrently.

Lithium

As with other serotonergic drugs, lithium may enhance the serotonergic effects of fluvoxamine and, therefore, the combination should be used with caution. Seizures have been reported with the co-administration of fluvoxamine maleate and lithium.

Lorazepam

A study of multiple doses of fluvoxamine maleate (50 mg bid) in healthy male volunteers (N=12) and a single dose of lorazepam (4 mg single dose) indicated no significant pharmacokinetic interaction. On average, both lorazepam alone and lorazepam with fluvoxamine produced substantial decrements in cognitive functioning; however, the co-administration of fluvoxamine and lorazepam did not produce larger mean decrements compared to lorazepam alone.

Methadone

Significantly increased methadone (plasma level:dose) ratios have been reported when fluvoxamine maleate was administered to patients receiving maintenance methadone treatment, with symptoms of opioid intoxication in one patient. Opioid withdrawal symptoms were reported following fluvoxamine maleate discontinuation in another patient.

Monoamine Oxidase Inhibitors

See WARNINGS

Serotonergic Drugs

Based on the mechanism of action of fluvoxamine and the potential for serotonin syndrome, caution is advised when fluvoxamine is coadministered with other drugs that may affect the serotonergic neurotransmitter systems, such as triptans, linezolid (an antibiotic which is a reversible non-selective MAOI), lithium, tramadol, or St. John's Wort (see WARNINGS – Serotonin Syndrome). The concomitant use of fluvoxamine with other SSRIs, SNRIs or tryptophan is not recommended (see PRECAUTIONS – Drug Interactions).

Sumatriptan

There have been rare postmarketing reports describing patients with weakness, hyperreflexia, and incoordination following the use of a selective serotonin reuptake inhibitor (SSRI) and sumatriptan. If concomitant treatment with sumatriptan and an SSRI (eg. fluoxetine, fluvoxamine, paroxetine, sertraline) is clinically warranted, appropriate observation of the patient is advised.

Tacrine

In a study of 13 healthy, male volunteers, a single 40 mg dose of tacrine added to fluvoxamine 100 mg/day administered at steady-state was associated with five- and eight-fold increases in tacrine Cmax and AUC, respectively, compared to the administration of tacrine alone. Five subjects experienced nausea, vomiting, sweating, and diarrhea following co-administration, consistent with the cholinergic effects of tacrine.

Thioridazine

See CONTRAINDICATIONS and WARNINGS

Tizanidine

See CONTRAINDICATIONS and WARNINGS

Tricyclic Antidepressants (TCAs)

Significantly increased plasma TCA levels have been reported with the co-administration of fluvoxamine maleate and amitriptyline, clomipramine or imipramine. Caution is indicated with the co-administration of Fluvoxamine Maleate Tablets and TCAs; plasma TCA concentrations may need to be monitored, and the dose of TCA may need to be reduced.

Triptans

There have been rare postmarketing reports of serotonin syndrome with use of an SSRI and a triptan. If concomitant treatment of fluvoxamine with a triptan is clinically warranted, careful observation of the patient is advised, particularly during treatment initiation and dose increases (see WARNINGS – Serotonin Syndrome).

Tryptophan

Tryptophan may enhance the serotonergic effects of fluvoxamine, and the combination should, therefore, be used with caution. Severe vomiting has been reported with the co-administration of fluvoxamine maleate and tryptophan.

Other Drugs

Drugs That Interfere With Hemostasis (NSAIDs, Aspirin, Warfarin, etc.)

Serotonin release by platelets plays an important role in hemostasis. Epidemiological studies of the case-control and cohort design that have demonstrated an association between use of psychotropic drugs that interfere with serotonin reuptake and the occurrence of upper gastrointestinal bleeding have also shown that concurrent use of an NSAID or aspirin potentiated the risk of bleeding. Thus, patients should be cautioned about the use of such drugs concurrently with fluvoxamine.

Theophylline

See WARNINGS

Warfarin

See WARNINGS

Alosetron

Because alosetron is metabolized by a variety of hepatic CYP drug-metabolizing enzymes, inducers or inhibitors of these enzymes may change the clearance of alosetron. Fluvoxamine is a known potent inhibitor of CYP1A2 and also inhibits CYP3A4, CYP2C9, and CYP2C19. In a pharmacokinetic study, 40 healthy female subjects received fluvoxamine in escalating doses from 50 to 200 mg a day for 16 days, with coadministration of alosetron 1 mg on the last day. Fluvoxamine increased mean alosetron plasma concentrations (AUC) approximately 6-fold and prolonged the half-life by approximately 3-fold. (See Contraindications, Precautions, and Lotronex™ (alosetron) package insert.)

Digoxin

Administration of fluvoxamine maleate 100 mg daily for 18 days (N=8) did not significantly affect the pharmacokinetics of a 1.25 mg single intravenous dose of digoxin.

Diltiazem

Bradycardia has been reported with the co-administration of fluvoxamine maleate and diltiazem.

Propranolol and Other Beta-Blockers

Co-administration of fluvoxamine maleate 100 mg per day and propranolol 160 mg per day in normal volunteers resulted in a mean five-fold increase (range 2 to 17) in minimum propranolol plasma concentrations. In this study, there was a slight potentiation of the propranolol-induced reduction in heart rate and reduction in the exercise diastolic pressure.

One case of bradycardia and hypotension and a second case of orthostatic hypotension have been reported with the co-administration of fluvoxamine and metoprolol.

If propranolol or metoprolol is co-administered with Fluvoxamine Maleate tablets, a reduction in the initial beta-blocker dose and more cautious dose titration is recommended. No dosage adjustment is required for Fluvoxamine Maleate Tablets.

Co-administration of fluvoxamine maleate 100 mg per day with atenolol 100 mg per day (N=6) did not affect the plasma concentrations of atenolol. Unlike propranolol and metoprolol which undergo hepatic metabolism, atenolol is eliminated primarily by renal excretion.

Effects of Smoking on Fluvoxamine Metabolism

Smokers had a 25% increase in the metabolism of fluvoxamine compared to nonsmokers.

Electroconvulsive Therapy (ECT)

There are no clinical studies establishing the benefits or risks of combined use of ECT and fluvoxamine maleate.

Carcinogenesis, Mutagenesis, and Impairment of Fertility

Carcinogenesis

There is no evidence of carcinogenicity, mutagenicity or impairment of fertility with fluvoxamine maleate.

There was no evidence of carcinogenicity in rats treated orally with fluvoxamine maleate for 30 months or hamsters treated orally with fluvoxamine maleate for 20 (females) or 26 (males) months. The daily doses in the high dose groups in these studies were increased over the course of the study from a minimum of 160 mg/kg to a maximum of 240 mg/kg in rats, and from a minimum of 135 mg/kg to a maximum of 240 mg/kg in hamsters. The maximum dose of 240 mg/kg is approximately 6 times the maximum human daily dose on a mg/m^2 basis.

Mutagenesis

No evidence of mutagenic potential was observed in a mouse micronucleus test, an in vitro chromosome aberration test, or the Ames microbial mutagen test with or without metabolic activation.

Impairment of Fertility

In fertility studies of male and female rats, up to 80 mg/kg/day orally of fluvoxamine maleate, (approximately 2 times the maximum human daily dose on a mg/m^2 basis) had no effect on mating performance, duration of gestation, or pregnancy rate.

Pregnancy

Teratogenic Effects

Pregnancy Category C

In teratology studies in rats and rabbits, daily oral doses of fluvoxamine maleate of up to 80 and 40 mg/kg, respectively (approximately 2 times the maximum human daily dose on a mg/m^2 basis) caused no fetal malformations. However, in other reproduction studies in which pregnant rats were dosed through weaning there was (1) an increase in pup mortality at birth (seen at 80 mg/kg and above but not at 20 mg/kg), and (2) decreases in postnatal pup weights (seen at 160 but not at 80 mg/kg) and survival (seen at all doses; lowest dose tested = 5 mg/kg). (Doses of 5, 20, 80, and 160 mg/kg are approximately 0.1, 0.5, 2, and 4 times the maximum human daily dose on a mg/m^2 basis.) While the results of a cross-fostering study implied that at least some of these results likely occurred secondarily to maternal toxicity, the role of a direct drug effect on the fetuses or pups could not be ruled out. There are no adequate and well-controlled studies in pregnant women. Fluvoxamine maleate should be used during pregnancy only if the potential benefit justifies the potential risk to the fetus.

Nonteratogenic Effects

Neonates exposed to fluvoxamine and other SSRIs or serotonin and norepinephrine reuptake inhibitors (SNRIs), late in the third trimester have developed complications requiring prolonged hospitalization, respiratory support, and tube feeding. These findings are based on postmarketing reports. Such complications can arise immediately upon delivery. Reported clinical findings have included respiratory distress, cyanosis, apnea, seizures, temperature instability, feeding difficulty, vomiting, hypoglycemia, hypotonia, hypertonia, hyperreflexia, tremor, jitteriness, irritability, and constant crying. These features are consistent with either a direct toxic effect of SSRIs and SNRIs or, possibly, a drug discontinuation syndrome. It should be noted that, in some cases, the clinical picture is consistent with serotonin syndrome (see WARNINGS).

Infants exposed to SSRIs in late pregnancy may have an increased risk for persistent pulmonary hypertension of the newborn (PPHN). PPHN is associated with substantial neonatal morbidity and mortality. In a case-control study of 377 women whose infants were born with PPHN and 836 women whose infants were born healthy, the risk for developing PPHN was approximately six-fold higher for infants exposed to SSRIs after the 20th week of gestation compared to infants who had not been exposed to antidepressants during pregnancy. PPHN occurs in 1-2 per 1000 live births in the general population.

When treating a pregnant woman with fluvoxamine during the third trimester, the physician should carefully consider both the potential risks and benefits of treatment (see DOSAGE AND ADMINISTRATION). Physicians should note that in a prospective longitudinal study of 201 women with a history of major depression who were euthymic at the beginning of pregnancy, women who discontinued antidepressant medication during pregnancy were more likely to experience a relapse of major depression than women who continued antidepressant medication.

Labor and Delivery

The effect of fluvoxamine on labor and delivery in humans is unknown.

Nursing Mothers

As for many other drugs, fluvoxamine is secreted in human breast milk. The decision of whether to discontinue nursing or to discontinue the drug should take into account the potential for serious adverse effects from exposure to fluvoxamine in the nursing infant as well as the potential benefits of Fluvoxamine Maleate Tablets therapy to the mother.

Pediatric Use

Safety and effectiveness in the pediatric population other than pediatric patients with OCD have not been established (see BOX WARNING and WARNINGS – Clinical Worsening and Suicide Risk). Anyone considering the use of Fluvoxamine in a child or adolescent must balance the potential risks with the clinical need.

The efficacy of fluvoxamine maleate for the treatment of OCD was demonstrated in a 10-week multicenter placebo controlled study with 120 outpatients ages 8-17. In addition, 99 of these outpatients continued open-label fluvoxamine maleate treatment for up to another one to three years, equivalent to 94 patient years. The adverse event profile observed in that study was generally similar to that observed in adult studies with fluvoxamine (See WARNINGS – Clinical Worsening and Suicide Risk, ADVERSE REACTIONS, and DOSAGE AND ADMINISTRATION).

Decreased appetite and weight loss have been observed in association with the use of fluvoxamine as well as other SSRIs. Consequently, regular monitoring of weight and growth is recommended if treatment of a child with an SSRI is to be continued long term.

The risks, if any that may be associated with fluvoxamine's extended use in children and adolescents with OCD have not been systematically assessed. The prescriber should be mindful that the evidence relied upon to conclude that fluvoxamine is safe for use in children and adolescents derives from relatively short term clinical studies and from extrapolation of experience gained with adult patients. In particular, there are no studies that directly evaluate the effects of long term fluvoxamine use on growth, development, and maturation of children and adolescents. Although there is no affirmative finding to suggest that fluvoxamine possesses a capacity to adversely affect growth, development or maturation, the absence of such findings is not compelling evidence of the absence of the potential of fluvoxamine to have adverse effects in chronic use.

Geriatric Use

Approximately 230 patients participating in controlled premarketing studies with Fluvoxamine Maleate Tablets were 65 years of age or over. No overall differences in safety were observed between these patients and younger patients. Other reported clinical experience has not identified differences in response between the elderly and younger patients. SSRIs and SNRIs, including fluvoxamine, have been associated with cases of clinically significant hyponatremia in elderly patients, who may be at greater risk for this adverse event (see PRECAUTIONS, Hyponatremia). Furthermore, the clearance of fluvoxamine is decreased by about 50% in elderly compared to younger patients (see Pharmacokinetics under CLINICAL PHARMACOLOGY), and greater sensitivity of some older individuals also cannot be ruled out. Consequently, Fluvoxamine Maleate Tablets should be slowly titrated during initiation of therapy.

ADVERSE REACTIONS

Associated with Discontinuation of Treatment

Of the 1087 OCD and depressed patients treated with fluvoxamine maleate in controlled clinical trials conducted in North America, 22% discontinued treatment due to an adverse event. The most common events (≥1%) associated with discontinuation and considered to be drug related (i.e., those events associated with dropout at a rate at least twice that of placebo) included:

Table 2 ADVERSE EVENTS ASSOCIATED WITH DISCONTINUATION OF TREATMENT IN OCD AND DEPRESSION POPULATIONS
BODY SYSTEM/ ADVERSE EVENT | PERCENTAGE OF PATIENTS
BODY SYSTEM/ ADVERSE EVENT | FLUVOXAMINE | PLACEBO
BODY AS A WHOLE
Headache | 3% | 1%
Asthenia | 2% | <1%
Abdominal Pain | 1% | 0%
DIGESTIVE
Nausea | 9% | 1%
Diarrhea | 1% | <1%
Vomiting | 2% | <1%
Anorexia | 1% | <1%
Dyspepsia | 1% | <1%
NERVOUS SYSTEM
Insomnia | 4% | 1%
Somnolence | 4% | <1%
Nervousness | 2% | <1%
Agitation | 2% | <1%
Dizziness | 2% | <1%
Anxiety | 1% | <1%
Dry mouth | 1% | <1%

Incidence in Controlled Trials

Commonly Observed Adverse Events in Controlled Clinical Trials

Fluvoxamine Maleate Tablets have been studied in controlled trials of OCD (N=320) and depression (N=1350).

In general, adverse event rates were similar in the two data sets as well as in the pediatric OCD study. The most commonly observed adverse events associated with the use of Fluvoxamine Maleate Tablets and likely to be drug-related (incidence of 5% or greater and at least twice that for placebo) derived from TABLE 2 were: somnolence, insomnia, nervousness, tremor, nausea, dyspepsia, anorexia, vomiting, abnormal ejaculation, asthenia, and sweating. In a pool of two studies involving only patients with OCD, the following additional events were identified using the above rule: dry mouth, decreased libido, urinary frequency, anorgasmia, rhinitis and taste perversion. In a study of pediatric patients with OCD, the following additional events were identified using the above rule: agitation, depression, dysmenorrhea, flatulence, hyperkinesia, and rash.

Adverse Events Occurring at an Incidence of 1%

Table 2 enumerates adverse events that occurred in adults at a frequency of 1% or more, and were more frequent than in the placebo group, among patients treated with Fluvoxamine Maleate Tablets in two short-term placebo controlled OCD trials (10 week) and depression trials (6 week) in which patients were dosed in a range of generally 100 to 300 mg/day.

This table shows the percentage of patients in each group who had at least one occurrence of an event at some time during their treatment. Reported adverse events were classified using a standard COSTART-based Dictionary terminology.

The prescriber should be aware that these figures cannot be used to predict the incidence of side effects in the course of usual medical practice where patient characteristics and other factors may differ from those that prevailed in the clinical trials. Similarly, the cited frequencies cannot be compared with figures obtained from other clinical investigations involving different treatments, uses, and investigators. The cited figures, however, do provide the prescribing physician with some basis for estimating the relative contribution of drug and non-drug factors to the side-effect incidence rate in the population studied.

Table 3 TREATMENT-EMERGENT ADVERSE EVENT INCIDENCE RATES BY BODY SYSTEM IN ADULT OCD AND DEPRESSION POPULATIONS COMBINED [Events for which fluvoxamine maleate incidence was equal to or less than placebo are not listed in the table above, but include the following: abdominal pain, abnormal dreams, appetite increase, back pain, chest pain, confusion, dysmenorrhea, fever, infection, leg cramps, migraine, myalgia, pain, paresthesia, pharyngitis, postural hypotension, pruritus, rash, rhinitis, thirst and tinnitus.]
 | Percentage Of Patients Reporting Event
BODY SYSTEM/ ADVERSE EVENT | FLUVOXAMINE | PLACEBO
BODY SYSTEM/ ADVERSE EVENT | N = 892 | N = 778
BODY AS WHOLE
Headache | 22 | 20
Asthenia | 14 | 6
Flu Syndrome | 3 | 2
Chills | 2 | 1
CARDIOVASCULAR
Palpitations | 3 | 2
DIGESTIVE SYSTEM
Nausea | 40 | 14
Diarrhea | 11 | 7
Constipation | 10 | 8
Dyspepsia | 10 | 5
Anorexia | 6 | 2
Vomiting | 5 | 2
Flatulence | 4 | 3
Tooth Disorder [Includes "toothache," "tooth extraction and abscess," and "caries."] | 3 | 1
Dysphagia | 2 | 1
NERVOUS SYSTEM
Somnolence | 22 | 8
Insomnia | 21 | 10
Dry Mouth | 14 | 10
Nervousness | 12 | 5
Dizziness | 11 | 6
Tremor | 5 | 1
Anxiety | 5 | 3
Vasodilatation [Mostly feeling warm, hot, or flushed.] | 3 | 1
Hypertonia | 2 | 1
Agitation | 2 | 1
Decreased Libido | 2 | 1
Depression | 2 | 1
CNS Stimulation | 2 | 1
RESPIRATORY SYSTEM
Upper Respiratory Infection | 9 | 5
Dyspnea | 2 | 1
Yawn | 2 | 0
SKIN
Sweating | 7 | 3
SPECIAL SENSES
Taste Perversion | 3 | 1
Amblyopia [Mostly "blurred vision."] | 3 | 2
UROGENITAL
Abnormal Ejaculation [Mostly "delayed ejaculation."] , [Incidence based on number of male patients.] | 8 | 1
Urinary Frequency | 3 | 2
Impotence | 2 | 1
Anorgasmia | 2 | 0
Urinary Retention | 1 | 0

Adverse Events in OCD Placebo Controlled Studies Which are Markedly Different (defined as at least a two-fold difference) in rate from the Pooled Event Rates in OCD and Depression Placebo Controlled Studies

The events in OCD studies with a two-fold decrease in rate compared to event rates in OCD and depression studies were dysphagia and amblyopia (mostly blurred vision). Additionally, there was an approximate 25% decrease in nausea.

The events in OCD studies with a two-fold increase in rate compared to event rates in OCD and depression studies were: asthenia, abnormal ejaculation (mostly delayed ejaculation), anxiety, infection, rhinitis, anorgasmia (in males), depression, libido decreased, pharyngitis, agitation, impotence, myoclonus/twitch, thirst, weight loss, leg cramps, myalgia and urinary retention. These events are listed in order of decreasing rates in the OCD trials.

Other Adverse Events in OCD Pediatric Population

In pediatric patients (N=57) treated with Fluvoxamine Maleate Tablets, the overall profile of adverse events was generally similar to that seen in adult studies, as shown in Table 2. However, the following adverse events, not appearing in Table 2, were reported in two or more of the pediatric patients and were more frequent with Fluvoxamine Maleate Tablets than with placebo: abnormal thinking, cough increase, dysmenorrhea, ecchymosis, emotional lability, epistaxis, hyperkinesia, infection, manic reaction, rash, sinusitis, and weight decrease.

Male and Female Sexual Dysfunction with SSRIs

Although changes in sexual desire, sexual performance and sexual satisfaction often occur as manifestations of a psychiatric disorder and with aging, they may also be a consequence of pharmacologic treatment. In particular, some evidence suggests that selective serotonin reuptake inhibitors (SSRIs) can cause such untoward sexual experiences.

Reliable estimates of the incidence and severity of untoward experiences involving sexual desire, performance and satisfaction are difficult to obtain, however, in part because patients and physicians may be reluctant to discuss them. Accordingly, estimates of the incidence of untoward sexual experience and performance cited in product labeling are likely to underestimate their actual incidence.

The table below displays the incidence of sexual side effects reported by at least 2% of patients taking Fluvoxamine Maleate Tablets in placebo controlled trials in depression and OCD.

Table 4 PERCENTAGE OF PATIENTS REPORTING SEXUAL ADVERSE EVENTS IN ADULT PLACEBO-CONTROLLED TRIALS IN OCD AND DEPRESSION
 | Fluvoxamine Maleate Tablets N=892 | Placebo N=778
Abnormal Ejaculation [Based on the number of male patients.] | 8% | 1%
Impotence | 2% | 1%
Decreased Libido | 2% | 1%
Anorgasmia | 2% | 0%

There are no adequate and well-controlled studies examining sexual dysfunction associated with fluvoxamine treatment.

Fluvoxamine treatment has been associated with several cases of priapism. In those cases with a known outcome, patients recovered without sequelae and upon discontinuation of fluvoxamine.

While it is difficult to know the precise risk of sexual dysfunction associated with the use of SSRIs, physicians should routinely inquire about such possible side effects.

Vital Sign Changes

Comparisons of fluvoxamine maleate and placebo groups in separate pools of short-term OCD and depression trials on (1) median change from baseline on various vital signs variables and on (2) incidence of patients meeting criteria for potentially important changes from baseline on various vital signs variables revealed no important differences between fluvoxamine maleate and placebo.

Laboratory Changes

Comparisons of fluvoxamine maleate and placebo groups in separate pools of short-term OCD and depression trials on (1) median change from baseline on various serum chemistry, hematology, and urinalysis variables and on (2) incidence of patients meeting criteria for potentially important changes from baseline on various serum chemistry, hematology, and urinalysis variables revealed no important differences between fluvoxamine maleate and placebo.

ECG Changes

Comparisons of fluvoxamine maleate and placebo groups in separate pools of short-term OCD and depression trials on (1) mean change from baseline on various ECG variables and on (2) incidence of patients meeting criteria for potentially important changes from baseline on various ECG variables revealed no important differences between fluvoxamine maleate and placebo.

Other Events Observed During the Premarketing Evaluation of Fluvoxamine Maleate Tablets

During premarketing clinical trials conducted in North America and Europe, multiple doses of fluvoxamine maleate were administered for a combined total of 2737 patient exposures in patients suffering OCD or Major Depressive Disorder. Untoward events associated with this exposure were recorded by clinical investigators using descriptive terminology of their own choosing. Consequently, it is not possible to provide a meaningful estimate of the proportion of individuals experiencing adverse events without first grouping similar types of untoward events into a limited (i.e., reduced) number of standard event categories.

In the tabulations which follow, a standard COSTART-based Dictionary terminology has been used to classify reported adverse events. If the COSTART term for an event was so general as to be uninformative, it was replaced with a more informative term. The frequencies presented, therefore, represent the proportion of the 2737 patient exposures to multiple doses of fluvoxamine maleate who experienced an event of the type cited on at least one occasion while receiving fluvoxamine maleate. All reported events are included in the list below, with the following exceptions: 1) those events already listed in Table 2, which tabulates incidence rates of common adverse experiences in placebo-controlled OCD and depression clinical trials, are excluded; 2) those events for which a drug cause was considered remote (i.e., neoplasia, gastrointestinal carcinoma, herpes simplex, herpes zoster, application site reaction, and unintended pregnancy) are omitted; and 3) events which were reported in only one patient and judged to not be potentially serious are not included. It is important to emphasize that, although the events reported did occur during treatment with fluvoxamine maleate, a causal relationship to fluvoxamine maleate has not been established.

Events are further classified within body system categories and enumerated in order of decreasing frequency using the following definitions: frequent adverse events are defined as those occurring on one or more occasions in at least 1/100 patients; infrequent adverse events are those occurring between 1/100 and 1/1000 patients; and rare adverse events are those occurring in less than 1/1000 patients.

Body as a Whole: Frequent: accidental injury, malaise; Infrequent: allergic reaction, neck pain, neck rigidity, overdose, photosensitivity reaction, suicide attempt; Rare: cyst, pelvic pain, sudden death.

Cardiovascular System: Frequent: hypertension, hypotension, syncope, tachycardia; Infrequent: angina pectoris, bradycardia, cardiomyopathy, cardiovascular disease, cold extremities, conduction delay, heart failure, myocardial infarction, pallor, pulse irregular, ST segment changes; Rare: AV block, cerebrovascular accident, coronary artery disease, embolus, pericarditis, phlebitis, pulmonary infarction, supraventricular extrasystoles.

Digestive System: Frequent: elevated liver transaminases; Infrequent: colitis, eructation, esophagitis, gastritis, gastroenteritis, gastrointestinal hemorrhage, gastrointestinal ulcer, gingivitis, glossitis, hemorrhoids, melena, rectal hemorrhage, stomatitis; Rare: biliary pain, cholecystitis, cholelithiasis, fecal incontinence, hematemesis, intestinal obstruction, jaundice.

Endocrine System: Infrequent: hypothyroidism; Rare: goiter

Hemic and Lymphatic Systems: Infrequent: anemia, ecchymosis, leukocytosis, lymphadenopathy, thrombocytopenia; Rare: leukopenia, purpura.

Metabolic and Nutritional Systems: Frequent: edema, weight gain, weight loss; Infrequent: dehydration, hypercholesterolemia; Rare: diabetes mellitus, hyperglycemia, hyperlipidemia, hypoglycemia, hypokalemia, lactate dehydrogenase increased.

Musculoskeletal System: Infrequent: arthralgia, arthritis, bursitis, generalized muscle spasm, myasthenia, tendinous contracture, tenosynovitis; Rare: arthrosis, myopathy, pathological fracture.

Nervous System: Frequent: amnesia, apathy, hyperkinesia, hypokinesia, manic reaction, myoclonus, psychotic reaction; Infrequent: agoraphobia, akathisia, ataxia, CNS depression, convulsion, delirium, delusion, depersonalization, drug dependence, dyskinesia, dystonia, emotional lability, euphoria, extrapyramidal syndrome, gait unsteady, hallucinations, hemiplegia, hostility, hypersomnia, hypochondriasis, hypotonia, hysteria, incoordination, increased salivation, increased libido, neuralgia, paralysis, paranoid reaction, phobia, psychosis, sleep disorder, stupor, twitching, vertigo; Rare: akinesia, coma, fibrillations, mutism, obsessions, reflexes decreased, slurred speech, tardive dyskinesia, torticollis, trismus, withdrawal syndrome.

Respiratory System: Frequent: cough increased, sinusitis; Infrequent: asthma, bronchitis, epistaxis, hoarseness, hyperventilation; Rare: apnea, congestion of upper airway, hemoptysis, hiccups, laryngismus, obstructive pulmonary disease, pneumonia.

Skin: Infrequent: acne, alopecia, dry skin, eczema, exfoliative dermatitis, furunculosis, seborrhea, skin discoloration, urticaria.

Special Senses: Infrequent: accommodation abnormal, conjunctivitis, deafness, diplopia, dry eyes, ear pain, eye pain, mydriasis, otitis media, parosmia, photophobia, taste loss, visual field defect; Rare: corneal ulcer, retinal detachment.

Urogenital System: Infrequent: anuria, breast pain, cystitis, delayed menstruation [Based on the number of females.] , dysuria, female lactation, hematuria, menopause, menorrhagia, metrorrhagia, nocturia, polyuria, premenstrual syndrome, urinary incontinence, urinary tract infection, urinary urgency, urination impaired, vaginal hemorrhage, vaginitis; Rare: kidney calculus, hematospermia [Based on the number of males.] , oliguria.

Postmarketing Reports

Voluntary reports of adverse events in patients taking Fluvoxamine Maleate Tablets that have been received since market introduction and are of unknown causal relationship to Fluvoxamine Maleate Tablets use include: ventricular tachycardia (including torsades de pointes), porphyria, toxic epidermal necrolysis, Stevens-Johnson syndrome, Henoch-Schoenlein purpura, bullous eruption, priapism, agranulocytosis, aplastic anemia, anaphylactic reaction, angioedema, vasculitis, hyponatremia, acute renal failure, hepatitis, pancreatitis, ileus, serotonin syndrome, neuropathy, laryngismus and severe akinesia with fever when fluvoxamine was co- administered with antipsychotic medication.

DRUG ABUSE AND DEPENDENCE

Controlled Substance Class

Fluvoxamine Maleate Tablets are not controlled substances.

Physical and Psychological Dependence

The potential for abuse, tolerance and physical dependence with fluvoxamine maleate has been studied in a nonhuman primate model. No evidence of dependency phenomena was found. The discontinuation effects of Fluvoxamine Maleate Tablets were not systematically evaluated in controlled clinical trials. Fluvoxamine Maleate Tablets were not systematically studied in clinical trials for potential for abuse, but there was no indication of drug-seeking behavior in clinical trials. It should be noted, however, that patients at risk for drug dependency were systematically excluded from investigational studies of fluvoxamine maleate. Generally, it is not possible to predict on the basis of preclinical or premarketing clinical experience the extent to which a CNS active drug will be misused, diverted, and/or abused once marketed.

Consequently, physicians should carefully evaluate patients for a history of drug abuse and follow such patients closely, observing them for signs of fluvoxamine maleate misuse or abuse (i.e., development of tolerance, incrementation of dose, drug-seeking behavior).

OVERDOSAGE

Human Experience

Worldwide exposure to fluvoxamine maleate includes over 45,000 patients treated in clinical trials and an estimated exposure of 23,000,000 patients treated during worldwide marketing experience (circa 1999). Of the 462 cases of deliberate or accidental overdose involving fluvoxamine maleate reported from this population, there were 44 deaths. Of these, six were in patients taking fluvoxamine maleate alone and the remaining 38 were in patients taking fluvoxamine maleate along with other drugs. Among non-fatal overdose cases, 373 patients had complete recovery, four patients experienced adverse sequelae of overdosage, to include persistent mydriasis, unsteady gait, kidney complications (from trauma associated with overdose), and bowel infarction requiring a hemicolectomy. In the remaining 41 patients, the outcome was unknown. The largest known ingestion of fluvoxamine maleate involved 12,000 mg (equivalent of 2-3 months' dosage). The patient fully recovered. However, ingestions as low as 1,400 mg have been associated with lethal outcome, indicating considerable prognostic variability.

Commonly (≥5%) observed adverse events associated with fluvoxamine maleate overdose include coma, hypokalemia, hypotension, nausea, respiratory difficulties, somnolence, tachycardia, and vomiting. Other notable signs and symptoms seen with fluvoxamine maleate overdose (single or mixed drugs) included bradycardia, ECG abnormalities (such as heart arrest, QT interval prolongation, first degree atrioventricular block, bundle branch block, and junctional rhythm), convulsions, tremor, diarrhea, and increased reflexes.

Management of Overdose

Treatment should consist of those general measures employed in the management of overdosage with any antidepressant.

Ensure an adequate airway, oxygenation, and ventilation. Monitor cardiac rhythm and vital signs. General supportive and symptomatic measures are also recommended. Induction of emesis is not recommended. Gastric lavage with large-bore orogastric tube with appropriate airway protection, if needed, may be indicated if performed soon after ingestion, or in symptomatic patients.

Activated charcoal should be administered. Due to the large volume of distribution of this drug, forced diuresis, dialysis, hemoperfusion, and exchange transfusion are unlikely to be of benefit. No specific antidotes for fluvoxamine are known.

A specific caution involves patients taking, or recently having taken, fluvoxamine who might ingest excessive quantities of a tricyclic antidepressant. In such a case, accumulation of the parent tricyclic and/or an active metabolite may increase the possibility of clinically significant sequelae and extend the time needed for close medical observation (see Tricyclic Antidepressants (TCAs) under PRECAUTIONS).

In managing overdosage, consider the possibility of multiple drug involvement. The physician should consider contacting a poison control center for additional information on the treatment of any overdose. Telephone numbers for certified poison control centers are listed in the Physicians' Desk Reference (PDR).

DOSAGE AND ADMINISTRATION

Dosage for Adults

The recommended starting dose for Fluvoxamine Maleate Tablets in adult patients is 50 mg, administered as a single daily dose at bedtime. In the controlled clinical trials establishing the effectiveness of Fluvoxamine Maleate Tablets in OCD, patients were titrated within a dose range of 100 to 300 mg/day. Consequently, the dose should be increased in 50 mg increments every 4 to 7 days, as tolerated, until maximum therapeutic benefit is achieved, not to exceed 300 mg per day. It is advisable that a total daily dose of more than 100 mg should be given in two divided doses. If the doses are not equal, the larger dose should be given at bedtime.

Dosage for Pediatric Population (children and adolescents)

The recommended starting dose for Fluvoxamine Maleate Tablets in pediatric populations (age 8-17 years) is 25 mg, administered as a single daily dose at bedtime. In a controlled clinical trial establishing the effectiveness of Fluvoxamine Maleate Tablets in OCD, pediatric patients (ages 8-17) were titrated within a dose range of 50 to 200 mg/day. Physicians should consider age and gender differences when dosing pediatric patients. The maximum dose in children up to age 11 should not exceed 200 mg/day. Therapeutic effect in female children may be achieved with lower doses. Dose adjustment in adolescents (up to the adult maximum dose of 300 mg) may be indicated to achieve therapeutic benefit. The dose should be increased in 25 mg increments every 4 to 7 days, as tolerated, until maximum therapeutic benefit is achieved. It is advisable that a total daily dose of more then 50 mg should be given in two divided doses. If the two divided doses are not equal, the larger dose should be given at bedtime.

Dosage for Elderly or Hepatically Impaired Patients

Elderly patients and those with hepatic impairment have been observed to have a decreased clearance of fluvoxamine maleate. Consequently, it may be appropriate to modify the initial dose and the subsequent dose titration for these patient groups.

Maintenance/Continuation Extended Treatment

Although the efficacy of Fluvoxamine Maleate Tablets beyond 10 weeks of dosing for OCD has not been documented in controlled trials, OCD is a chronic condition, and it is reasonable to consider continuation for a responding patient. Dosage adjustments should be made to maintain the patient on the lowest effective dosage, and patients should be periodically reassessed to determine the need for continued treatment.

Treatment of Pregnant Women During the Third Trimester

Neonates exposed to fluvoxamine maleate tablets and other SSRIs or SNRIs late in the third trimester have developed complications requiring prolonged hospitalization, respiratory support, and tube feeding (see PRECAUTIONS). When treating pregnant women with fluvoxamine maleate tablets during the third trimester, the physician should carefully consider the potential risks and benefits of treatment. The physician may consider tapering fluvoxamine maleate tablets in the third trimester.

Discontinuation of Treatment with Fluvoxamine Maleate Tablets

Symptoms associated with discontinuation of other SSRIs and SNRIs have been reported (see PRECAUTIONS). Patients should be monitored for these symptoms when discontinuing treatment. A gradual reduction in the dose rather than abrupt cessation is recommended whenever possible. If intolerable symptoms occur following a decrease in the dose or upon discontinuation of treatment, then resuming the previously prescribed dose may be considered. Subsequently, the physician may continue decreasing the dose but at a more gradual rate.

HOW SUPPLIED

Tablets 25 mg: White to off-white, round, biconvex, film-coated tablets. The tablets are unscored and embossed with FLM 25" on one side.

Bottles of 30................................................................ NDC 063672-1025-1
Bottles of 100.............................................................. NDC 063672-1025-2
Bottles of 500.............................................................. NDC 063672-1025-4

Tablets 50 mg: White to off-white, round, biconvex, film-coated tablets. The tablets are scored on both sides and embossed with FLM 50" on one side.

Bottles of 30................................................................ NDC 063672-1050-1
Bottles of 100.............................................................. NDC 063672-1050-2
Bottles of 500.............................................................. NDC 063672-1050-4

Tablets 100 mg: White to off-white, round, biconvex, film-coated tablets. The tablets are scored on both sides and embossed with FLM 100" on one side.

Bottles of 30................................................................ NDC 063672-1100-1
Bottles of 100.............................................................. NDC 063672-1100-2
Bottles of 250.............................................................. NDC 063672-1100-3

STORAGE AND HANDLING

Fluvoxamine Maleate Tablets should be protected from high humidity and stored at controlled room temperature, 15°-30° C (59°- 86° F).

Dispense in tight containers.

Rx only

Synthon Pharmaceuticals, Inc.
Research Triangle Park, North Carolina 27709

PI-1000-9
Issued: 8/2007

Lotronex™ is a registered trademark of GlaxoSmithKline

SUPPLEMENTAL PATIENT MATERIAL

Medication Guide

Antidepressant Medicines, Depression and other Serious Mental Illnesses, and Suicidal Thoughts or Actions

Read the Medication Guide that comes with you or your family member's antidepressant medicine. This Medication Guide is only about the risk of suicidal thoughts and actions with antidepressant medicines. Talk to your, or your family member's, healthcare provider about:

- all risks and benefits of treatment with antidepressant medicines
- all treatment choices for depression or other serious mental illness

What is the most important information I should know about antidepressant medicines, depression and other serious mental illnesses, and suicidal thoughts or actions?

1. Antidepressant medicines may increase suicidal thoughts or actions in some children, teenagers, and young adults within the first few months of treatment.
2. Depression and other serious mental illnesses are the most important causes of suicidal thoughts and actions. Some people may have a particularly high risk of having suicidal thoughts or actions. These include people who have (or have a family history of) bipolar illness (also called manic-depressive illness) or suicidal thoughts or actions.
3. How can I watch for and try to prevent suicidal thoughts and actions in myself or a family member?
  - Pay close attention to any changes, especially sudden changes, in mood, behaviors, thoughts, or feelings. This is very important when an antidepressant medicine is started or when the dose is changed.
  - Call the healthcare provider right away to report new or sudden changes in mood, behavior, thoughts, or feelings.
  - Keep all follow-up visits with the healthcare provider as scheduled. Call the healthcare provider between visits as needed, especially if you have concerns about symptoms.

Call a healthcare provider right away if you or your family member has any of the following symptoms, especially if they are new, worse, or worry you:

- thoughts about suicide or dying
- attempts to commit suicide
- new or worse depression
- new or worse anxiety
- feeling very agitated or restless
- panic attacks
- trouble sleeping (insomnia)
- new or worse irritability
- acting aggressive, being angry, or violent
- acting on dangerous impulses
- an extreme increase in activity and talking (mania)
- other unusual changes in behavior or mood

What else do I need to know about antidepressant medicines?

- Never stop an antidepressant medicine without first talking to a healthcare provider. Stopping an antidepressant medicine suddenly can cause other symptoms.
- Antidepressants are medicines used to treat depression and other illnesses. It is important to discuss all the risks of treating depression and also the risks of not treating it. Patients and their families or other caregivers should discuss all treatment choices with the healthcare provider, not just the use of antidepressants.
- Antidepressant medicines have other side effects. Talk to the healthcare provider about the side effects of the medicine prescribed for you or your family member.
- Antidepressant medicines can interact with other medicines. Know all of the medicines that you or your family member takes. Keep a list of all medicines to show the healthcare provider. Do not start new medicines without first checking with your healthcare provider.
- Not all antidepressant medicines prescribed for children are FDA approved for use in children. Talk to your child's healthcare provider for more information.

This Medication Guide has been approved by the U.S. Food and Drug Administration for all antidepressants.